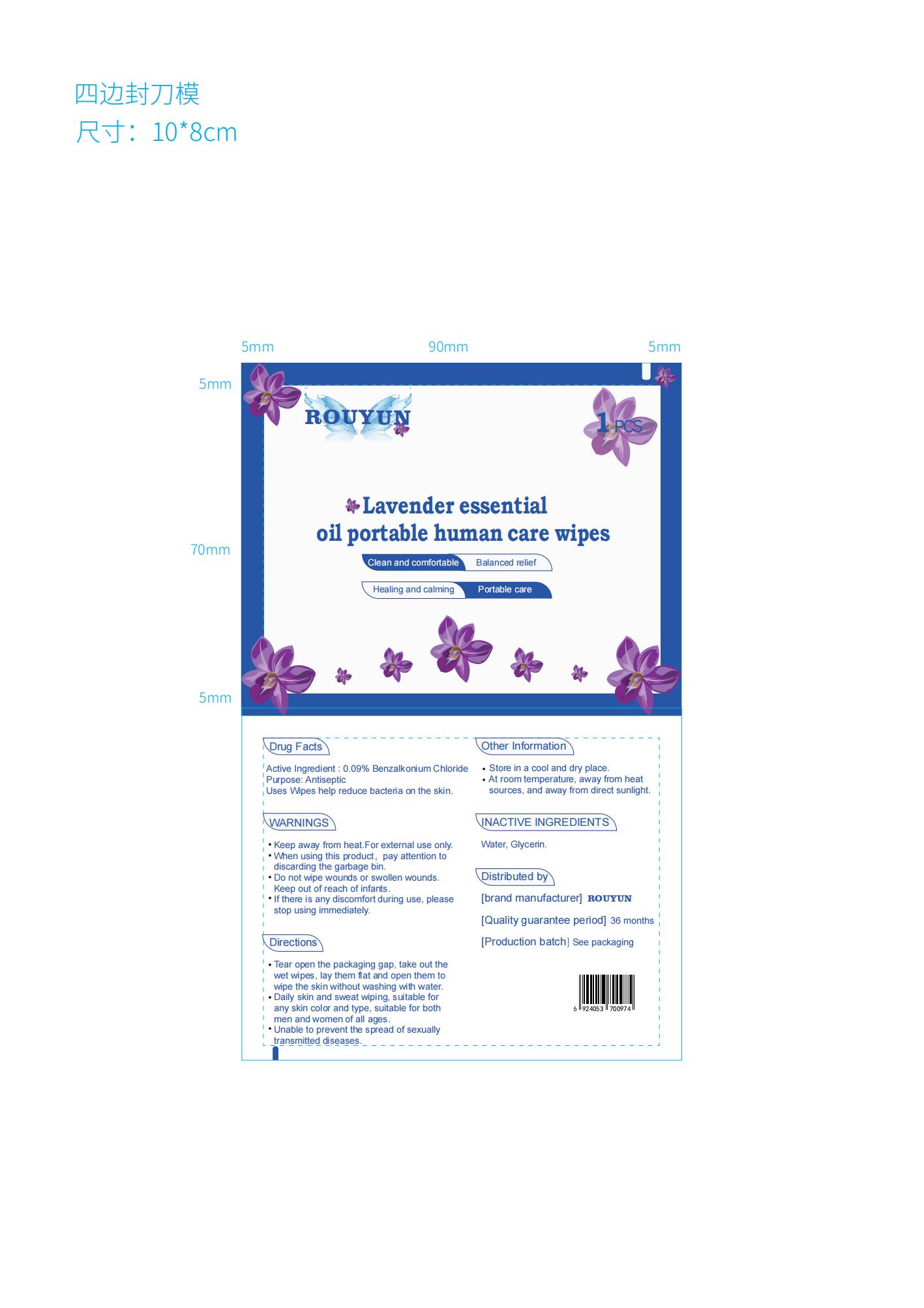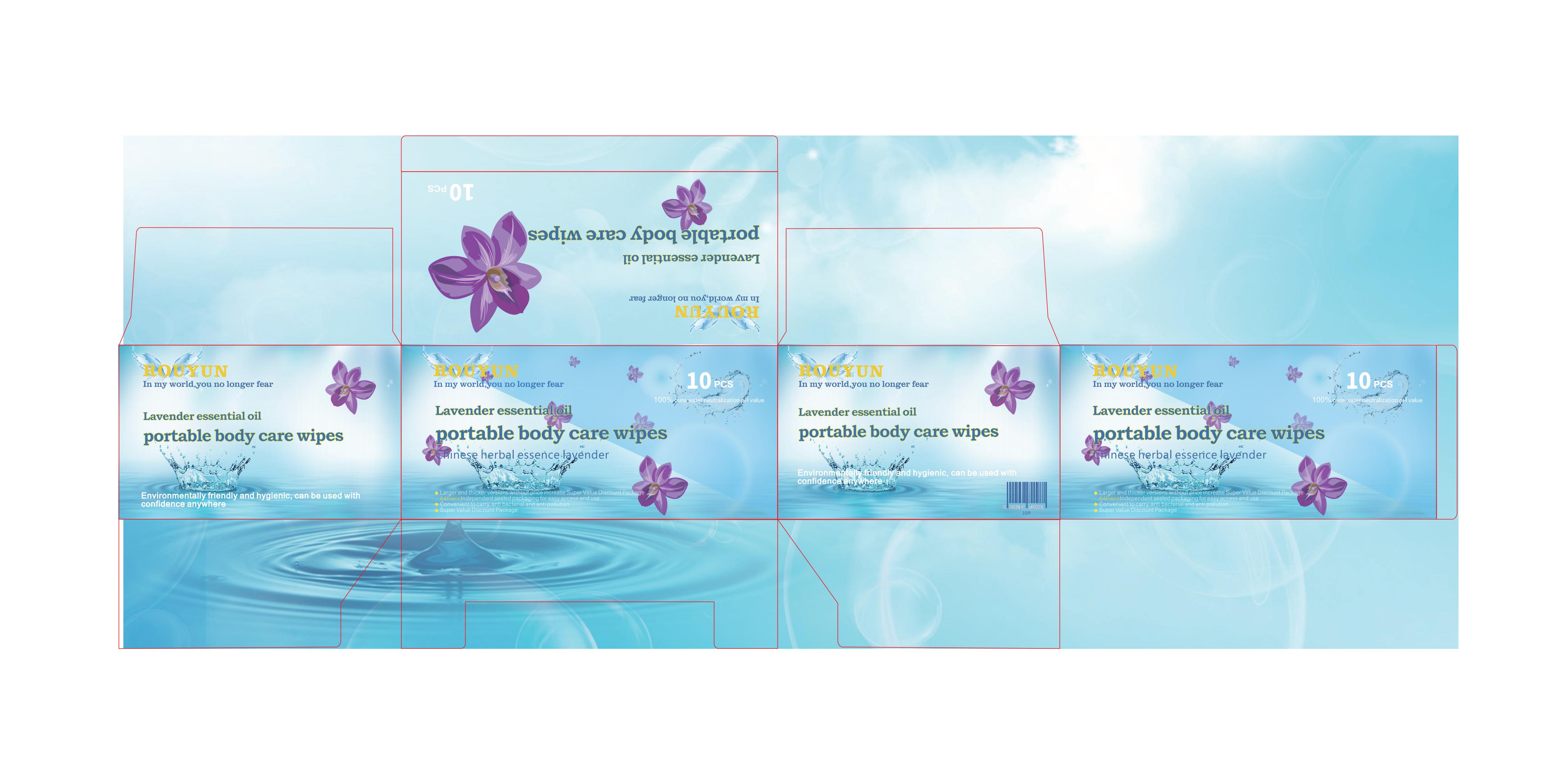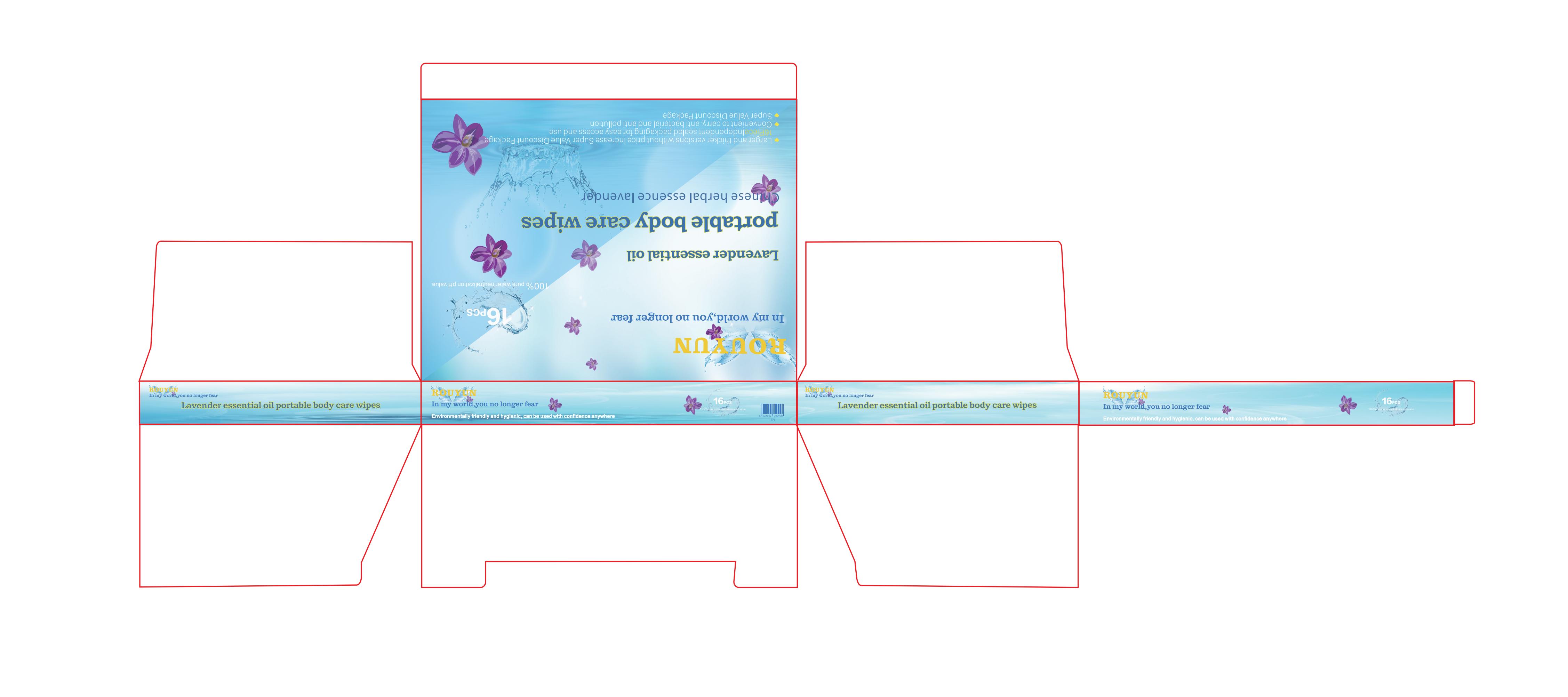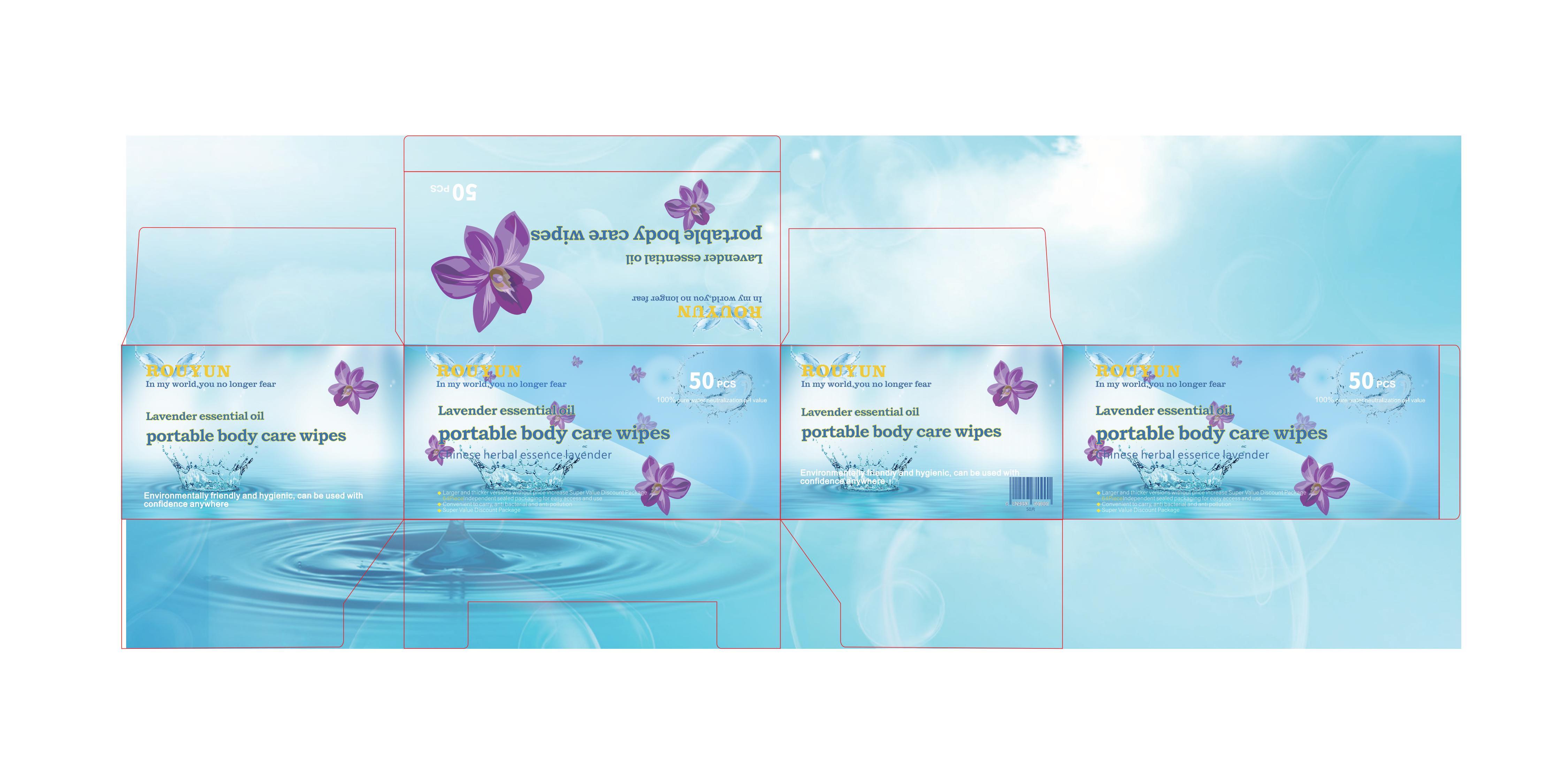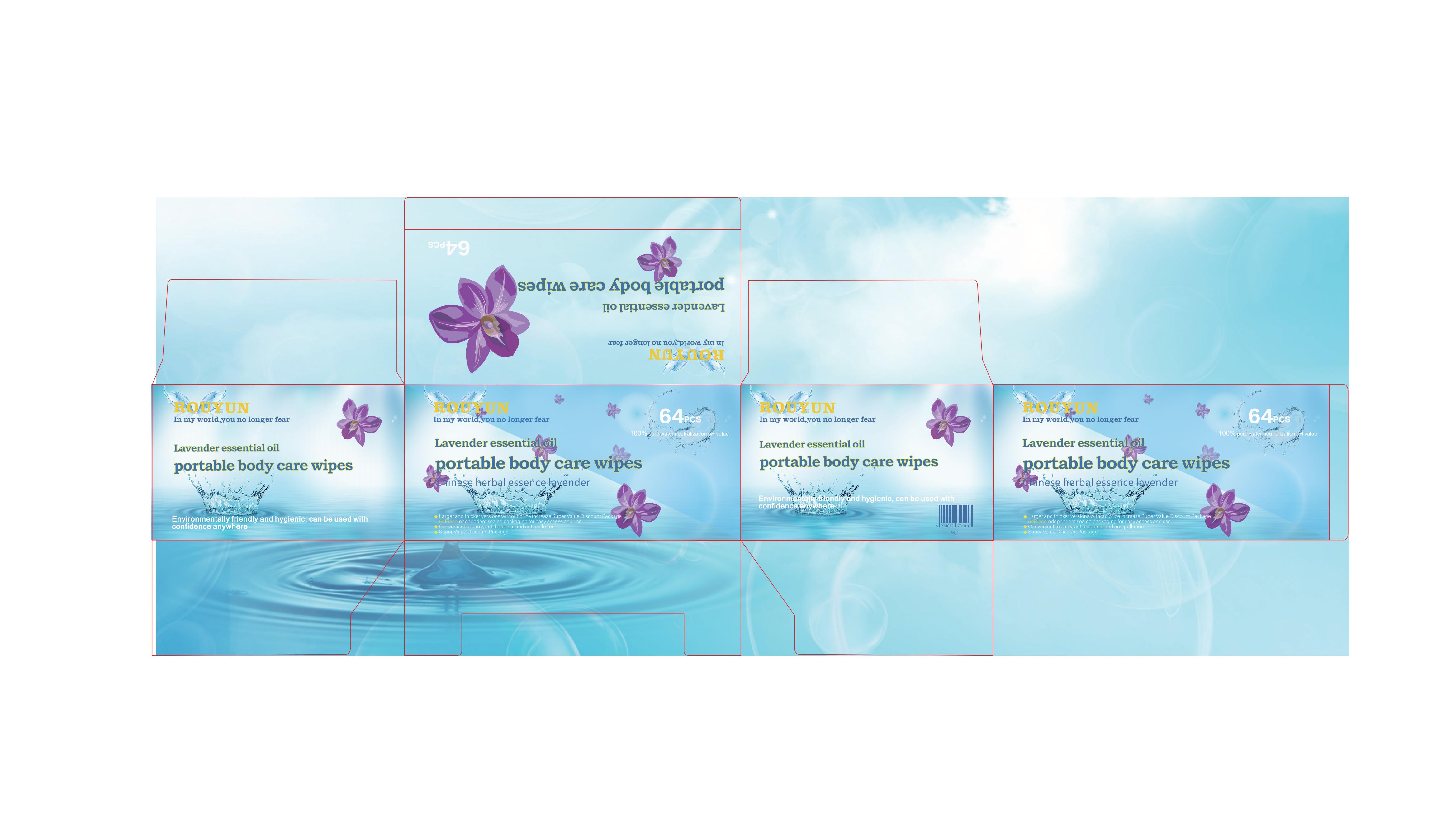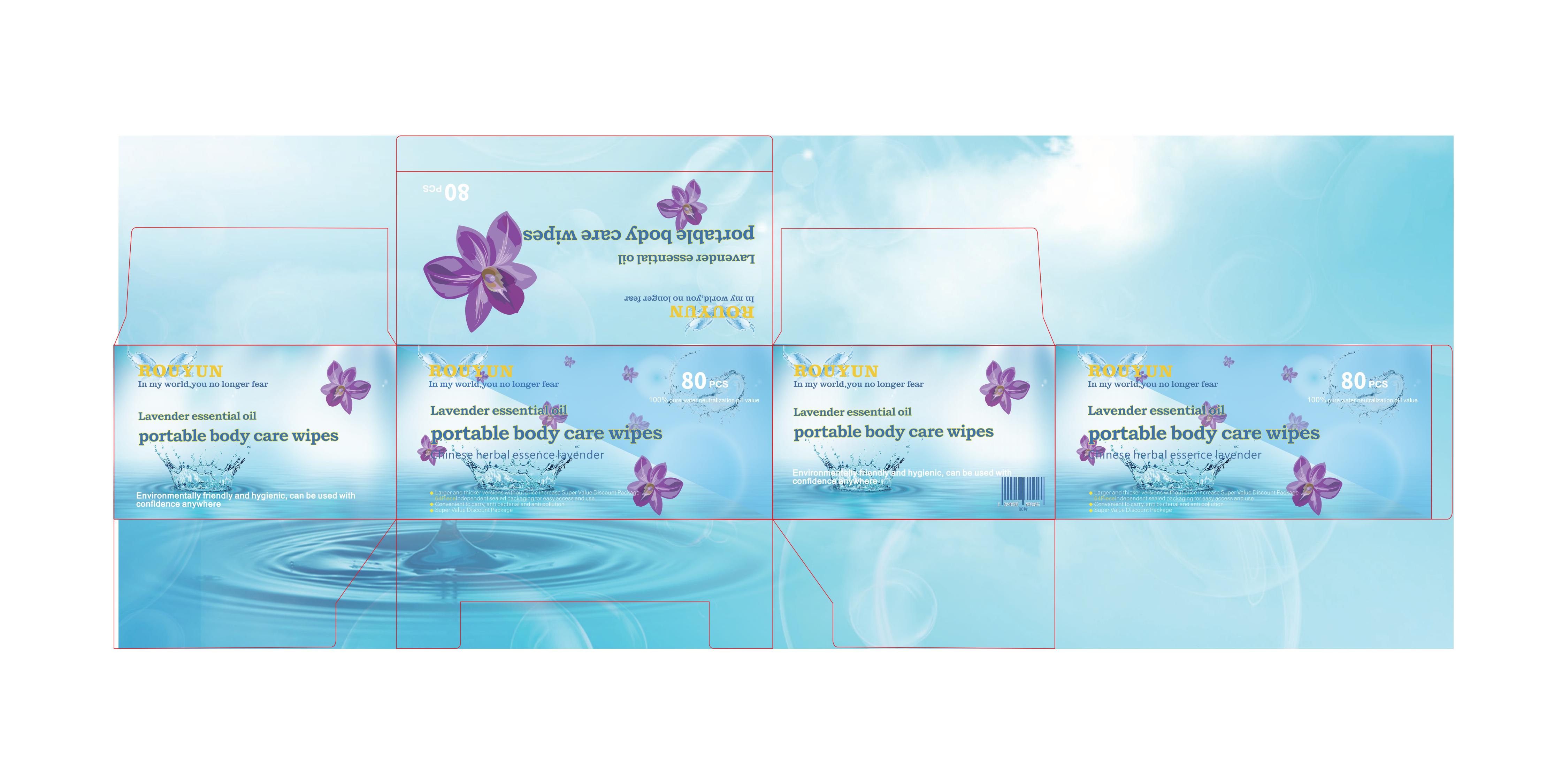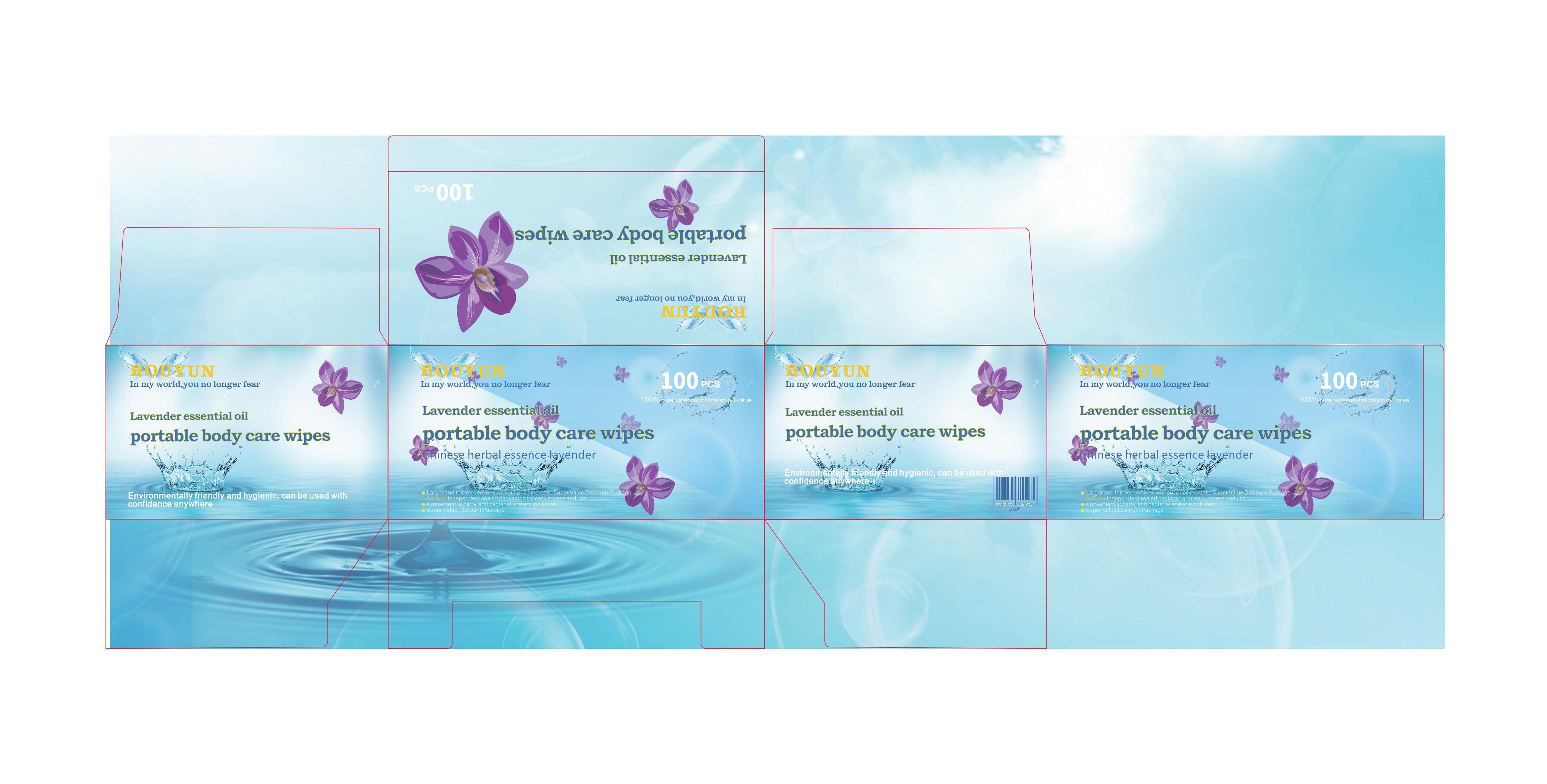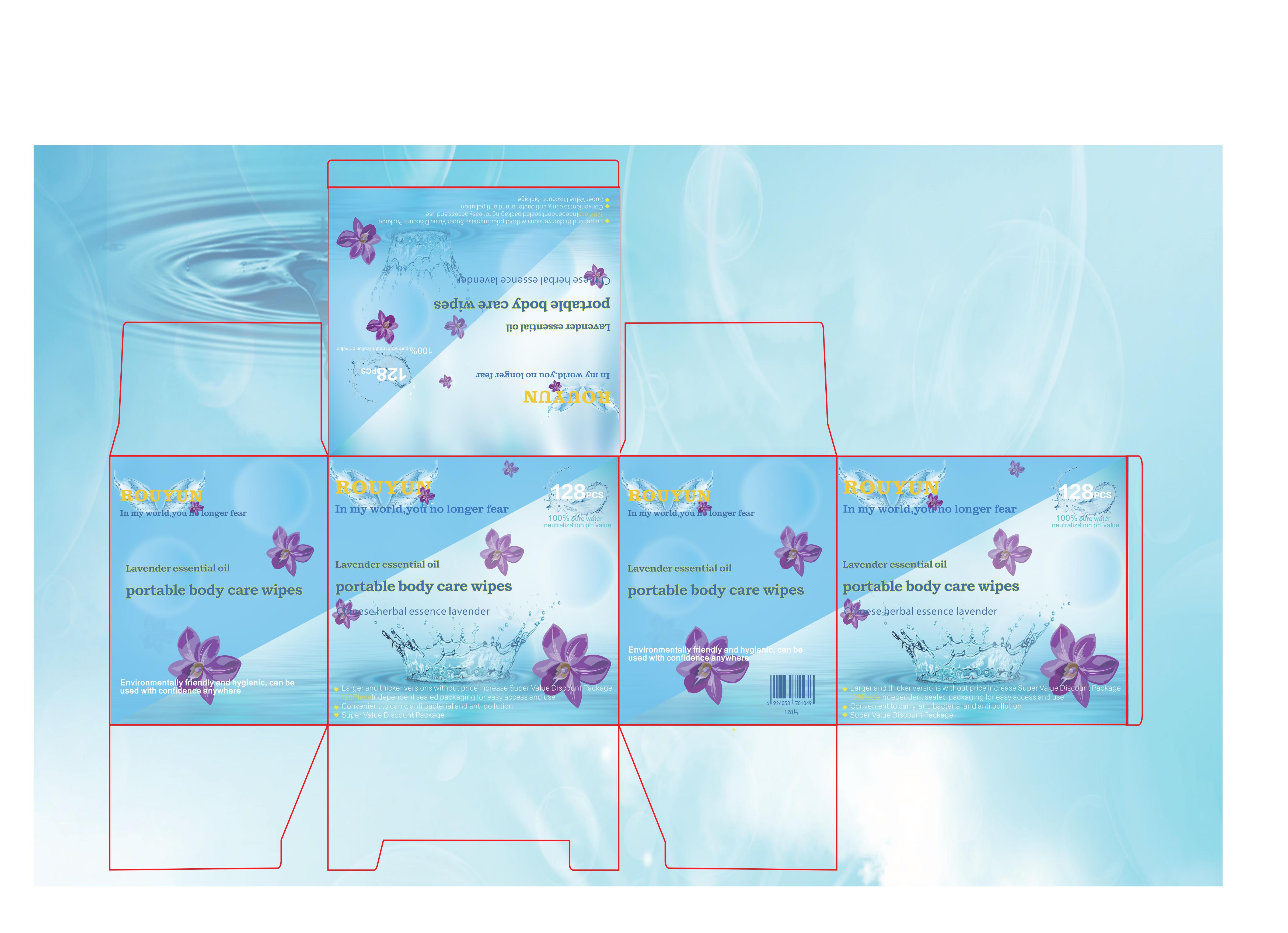 DRUG LABEL: ROUYUN Lavender essential oil portable body care wipes
NDC: 43116-033 | Form: CLOTH
Manufacturer: Shenzhen Shierjie Biological Engineering Co., LTD
Category: otc | Type: HUMAN OTC DRUG LABEL
Date: 20231218

ACTIVE INGREDIENTS: BENZALKONIUM CHLORIDE 0.09 g/100 1
INACTIVE INGREDIENTS: WATER; GLYCERIN

43116-033

Active Ingredient

Benzalkonium Chloride 0.09%

Purpose

Antiseptic

Use

Uses Wipes help reduce bacteria on the skin.

Warnings

Keep away from heat.For external use only.

Do not use

Do not wipe wounds or swollen wounds.

When Using

pay attention to discarding the garbage bin.

Stop Use

If there is any discomfort during use, please stop using immediately.

Ask Doctor

If there is any discomfort during use, please stop using immediately.

Keep Oot Of Reach Of Children

Keep out of reach of infants.

Directions

Tear open the packaging gap, take out the wet wipes, lay them flat and open them to wipe the skin without washing with water.
Daily skin and sweat wiping, suitable for any skin color and type, suitable for both men and women of all ages.
Unable to prevent the spread of sexually transmitted diseases.

Other information

Store in a cool and dry place.At room temperature, away from heat sources, and away from direct sunlight.

Inactive ingredients

Water, Glycerin.